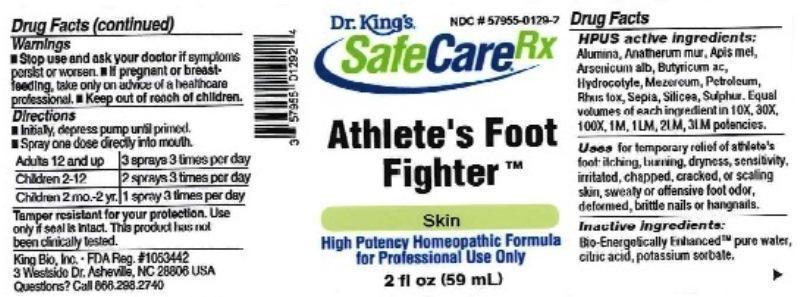 DRUG LABEL: Athletes Foot Fighter
NDC: 57955-0129 | Form: LIQUID
Manufacturer: King Bio Inc.
Category: homeopathic | Type: HUMAN OTC DRUG LABEL
Date: 20161213

ACTIVE INGREDIENTS: ALUMINUM OXIDE 10 [hp_X]/59 mL; CHRYSOPOGON ZIZANIOIDES ROOT 10 [hp_X]/59 mL; APIS MELLIFERA 10 [hp_X]/59 mL; ARSENIC TRIOXIDE 10 [hp_X]/59 mL; BUTYRIC ACID 10 [hp_X]/59 mL; CENTELLA ASIATICA 10 [hp_X]/59 mL; DAPHNE MEZEREUM BARK 10 [hp_X]/59 mL; KEROSENE 10 [hp_X]/59 mL; TOXICODENDRON PUBESCENS LEAF 10 [hp_X]/59 mL; SEPIA OFFICINALIS JUICE 10 [hp_X]/59 mL; SILICON DIOXIDE 10 [hp_X]/59 mL; SULFUR 10 [hp_X]/59 mL
INACTIVE INGREDIENTS: WATER; ANHYDROUS CITRIC ACID; POTASSIUM SORBATE

Athlete's Foot Fighter

ACTIVE INGREDIENT

Drug Facts__________________________________________________________________________________________________________

HPUS active ingredients: Alumina, Anatherum muricatum, Apis mellifica, Arsenicum album, Butyricum acidum, Hydrocotyle asiatica, Mezereum, Petroleum, Rhus toxicodendron, Sepia, Silicea, Sulphur. Equal volumes of each ingredient in 10X, 30X, 100X, 1M, 1LM, 2LM, 3LM potencies.

INDICATIONS AND USAGE

Uses for temporary relief of athlete's foot: itching, burning, dryness, sensitivity, irritated, chapped, cracked, or scaling skin, sweaty or offensive foot odor, deformed, brittle nails or hangnails.

Inactive Ingredients:

Bio-Energetically Enhanced™ pure water, citric acid and potassium sorbate.

Warnings

- Stop use and ask your doctor if symptoms persist or worsen.
- If pregnant or breast-feeding, take only on advice of a healthcare professional.

- Keep out of reach of children.

Directions

- Initially, depress pump until primed.
- Spray one dose directly into mouth.
- Adults 12 and up: 3 sprays 3 times per day.
- Children 2-12: 2 sprays 3 times per day.
- Children 2 mo.-2 y.r: 1 spray 3 times per day.

OTHER SAFETY INFORMATION

Tamper resistant for your protection. Use only if safety seal is intact. This product has not been clinically tested.

PURPOSE

Uses for temporary relief of athlete's foot:

- itching
- burning
- dryness
- sensitivity
- irritated
- chapped
- cracked
- scaling skin
- sweaty or offensive foot odor
- deformed, brittle nails or hangnails